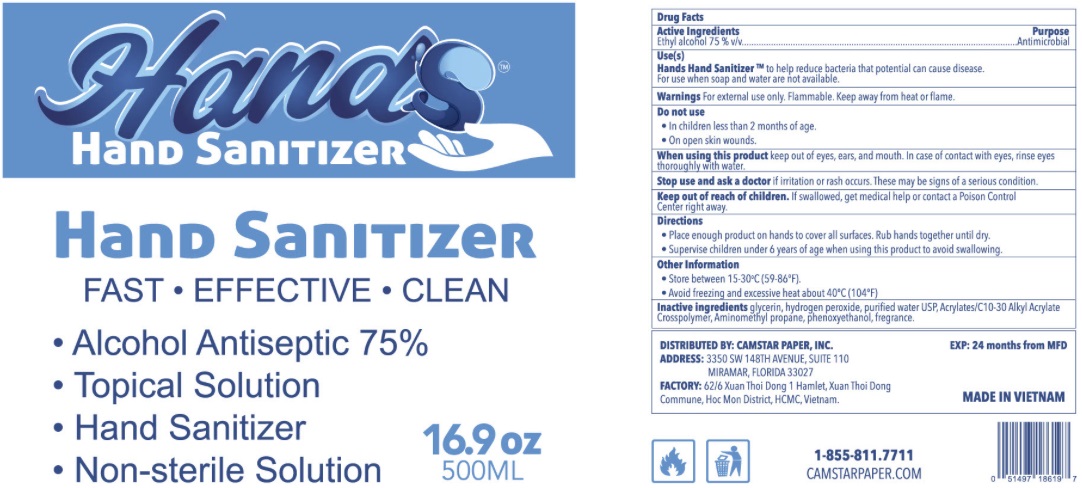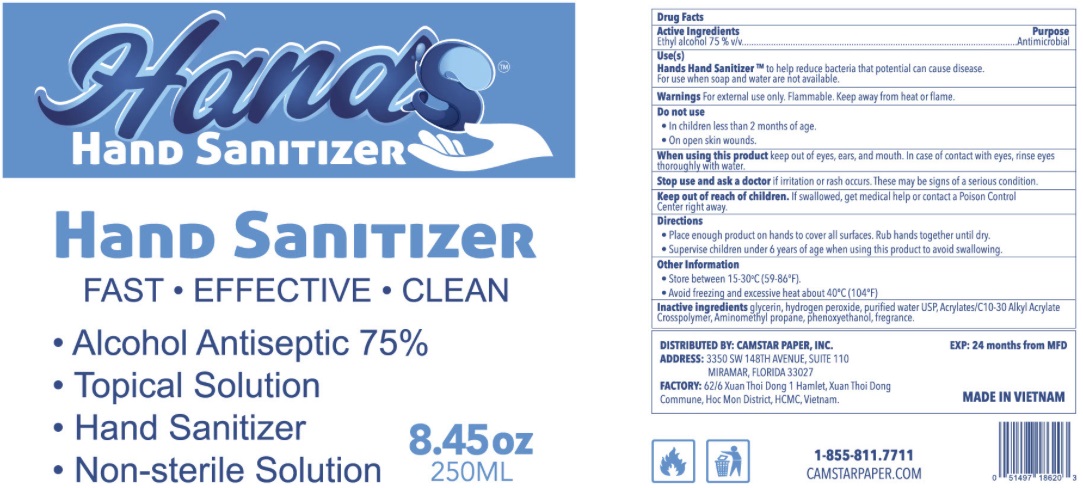 DRUG LABEL: HANDS Hand Sanitizer
NDC: 79792-000 | Form: GEL
Manufacturer: Camstar Paper Inc.
Category: otc | Type: HUMAN OTC DRUG LABEL
Date: 20200810

ACTIVE INGREDIENTS: ALCOHOL 0.75 mL/1 mL
INACTIVE INGREDIENTS: GLYCERIN; HYDROGEN PEROXIDE; WATER; CARBOMER INTERPOLYMER TYPE A (ALLYL SUCROSE CROSSLINKED); AMINOMETHYL PROPANEDIOL; PHENOXYETHANOL

HANDS Hand Sanitizer Gel

Active Ingredients

Ethyl alcohol 75 % v/v

Purpose

Antimicrobial

Use(s)

Hands Hand Sanitizer to help reduce bacteria that potential can cause disease. For use when soap and water are not available.

Warnings

For external use only. Flammable. Keep away from heat or flame.

Do not use

- in children less than 2 months of age.
- On open skin wounds.

When using this product

keep out of eyes, ears, and mouth. In case of contact with eyes, rinse eyes thoroughly with water.

Stop use and ask a doctor

if irritation or rash occurs. These may be signs of a serious condition.

Keep out of reach of children.

If swallowed, get medical help or contact a Poison Control Center right away.

Directions

Place enough product on hands to cover all surfaces. Rub hands together until dry.

Supervise children under 6 years of age when using this product to avoid swallowing.

Other Information

- Store between 15-30°C(59-86°F).
- Avoid freezing and excessive heat about 40°C (104°F)

Inactive ingredients

glycerin, hydrogen peroxide, purified water USP, Acrylates/C10-30 Alkyl Acrylate Crosspolymer, Aminomethyl Propane, Phenoxyethanol, fragrance.